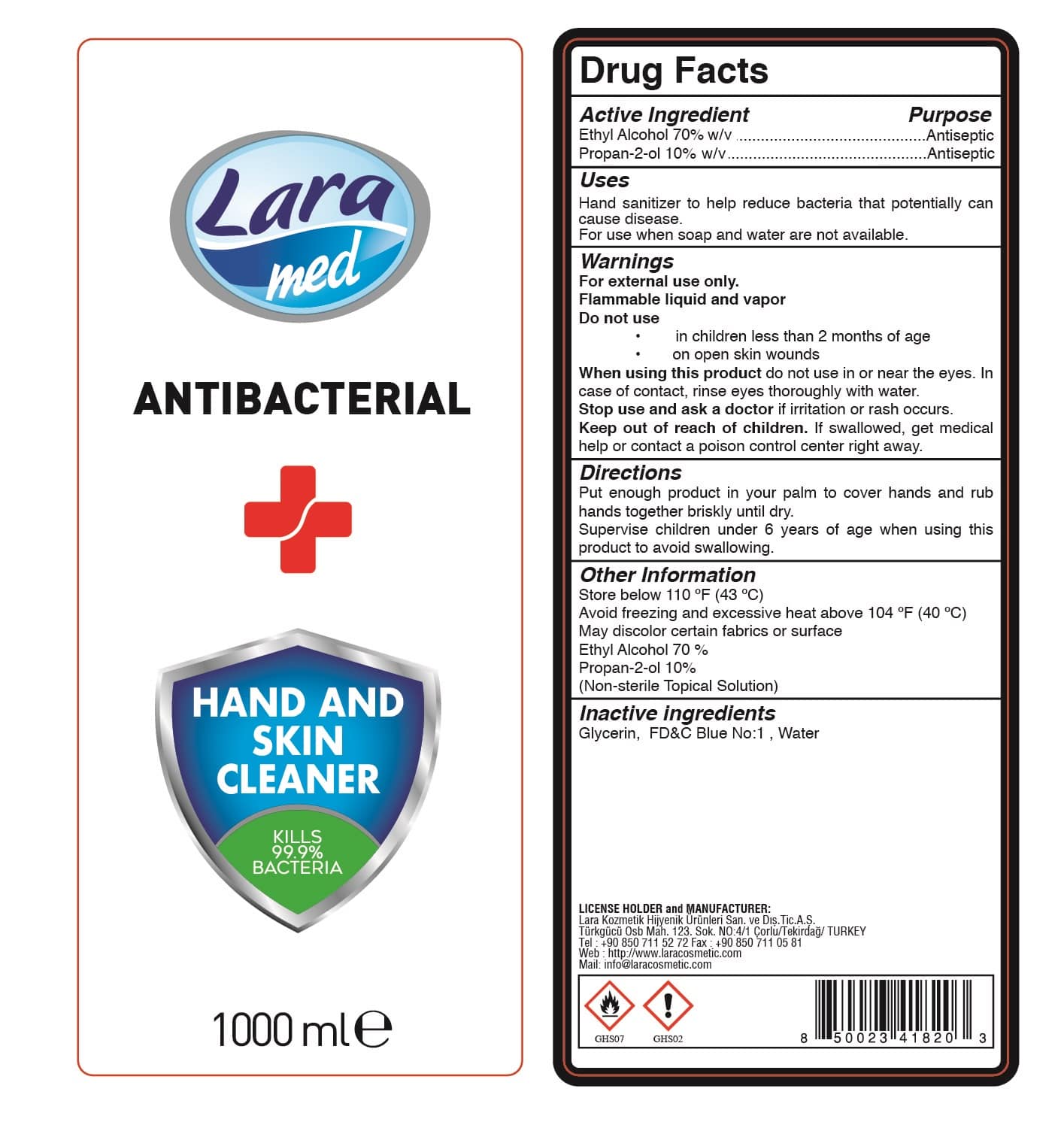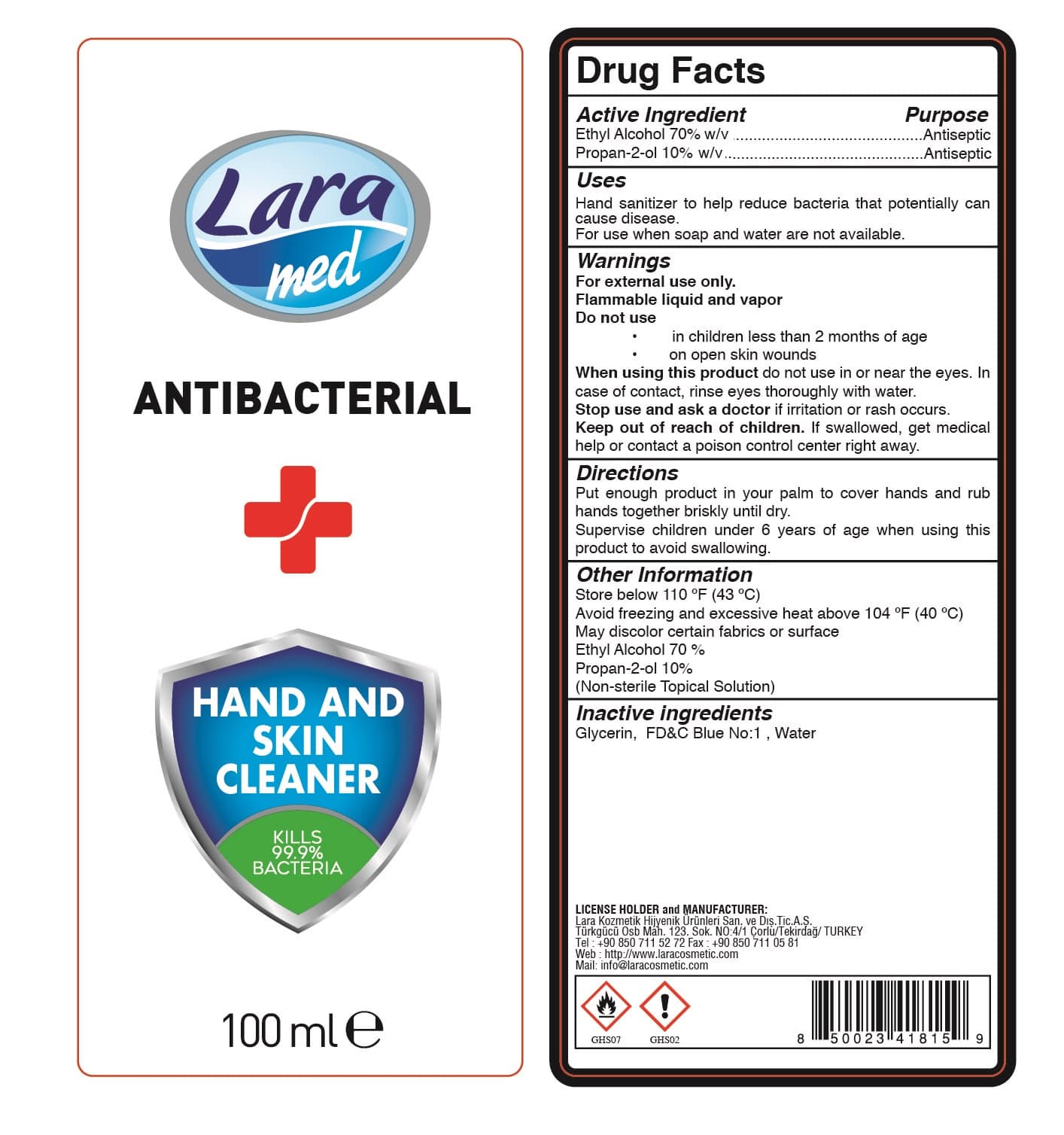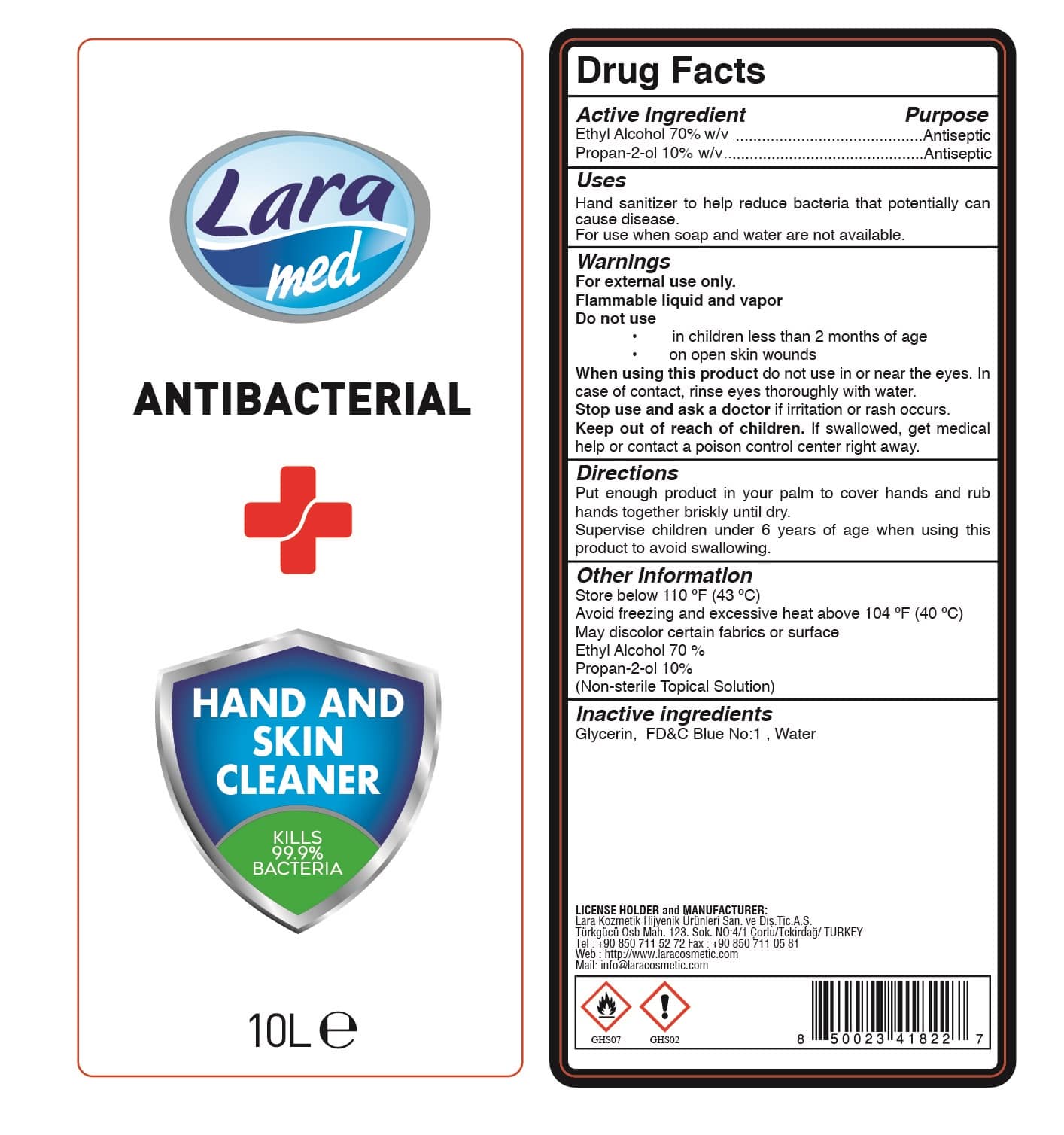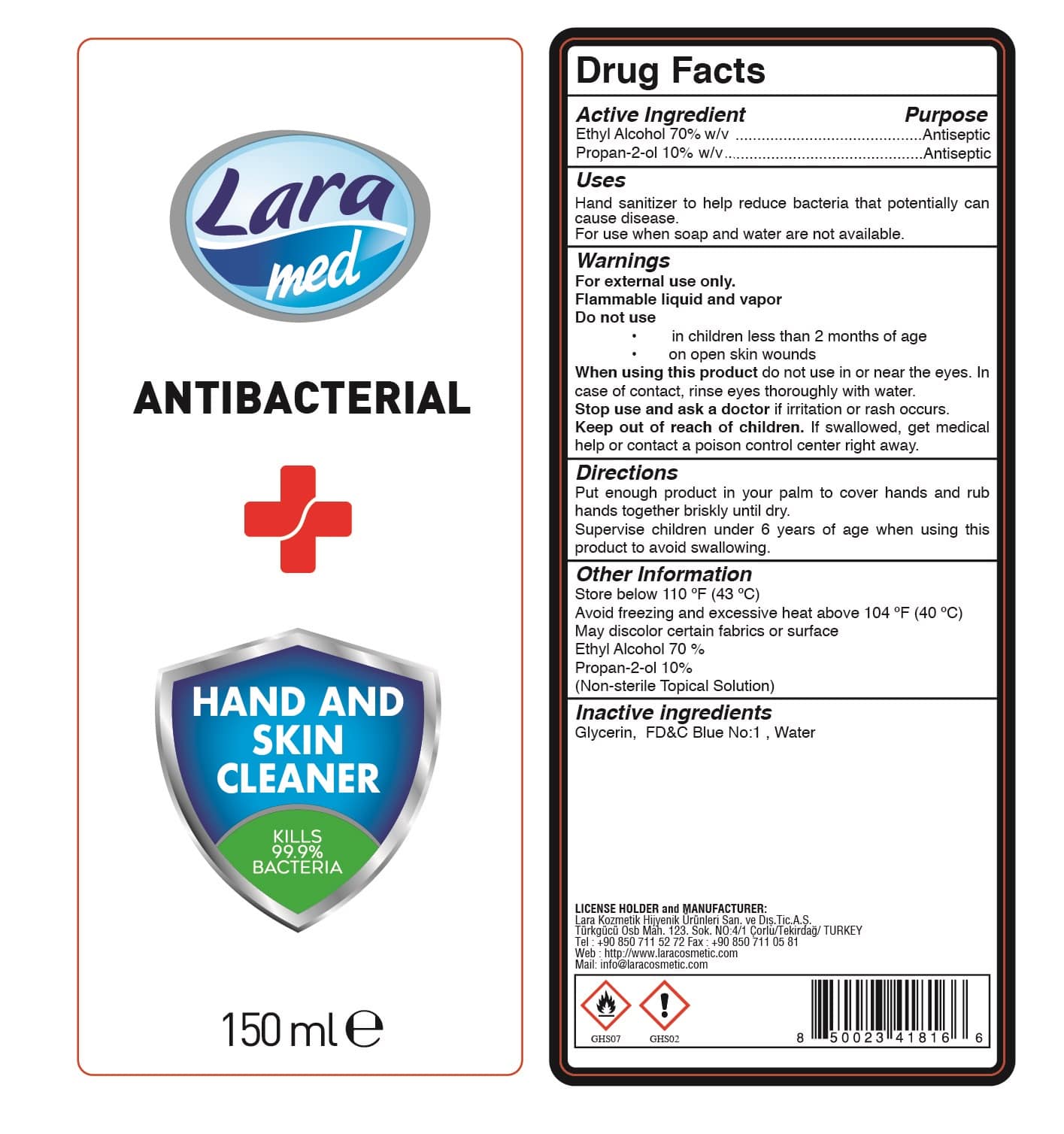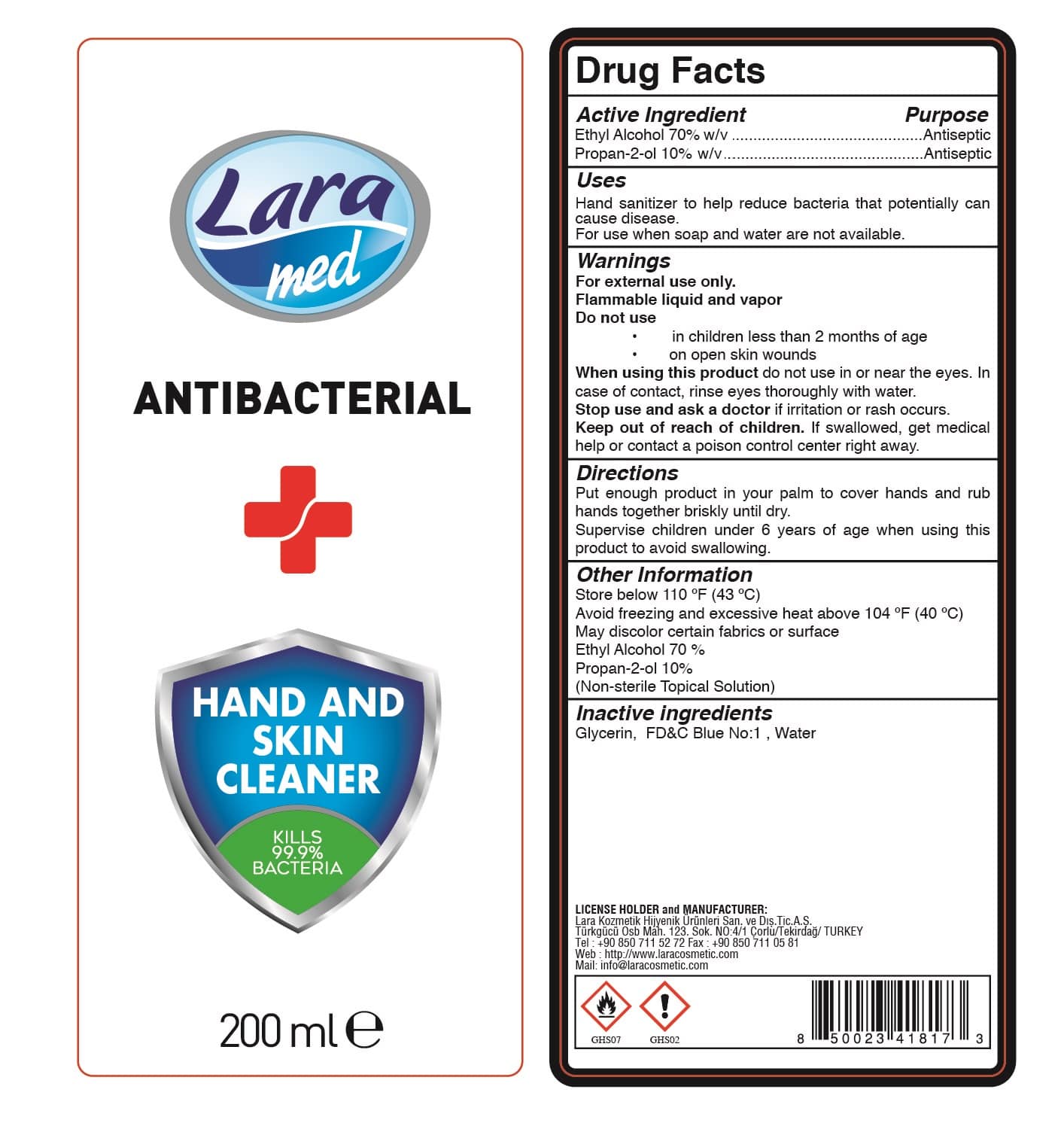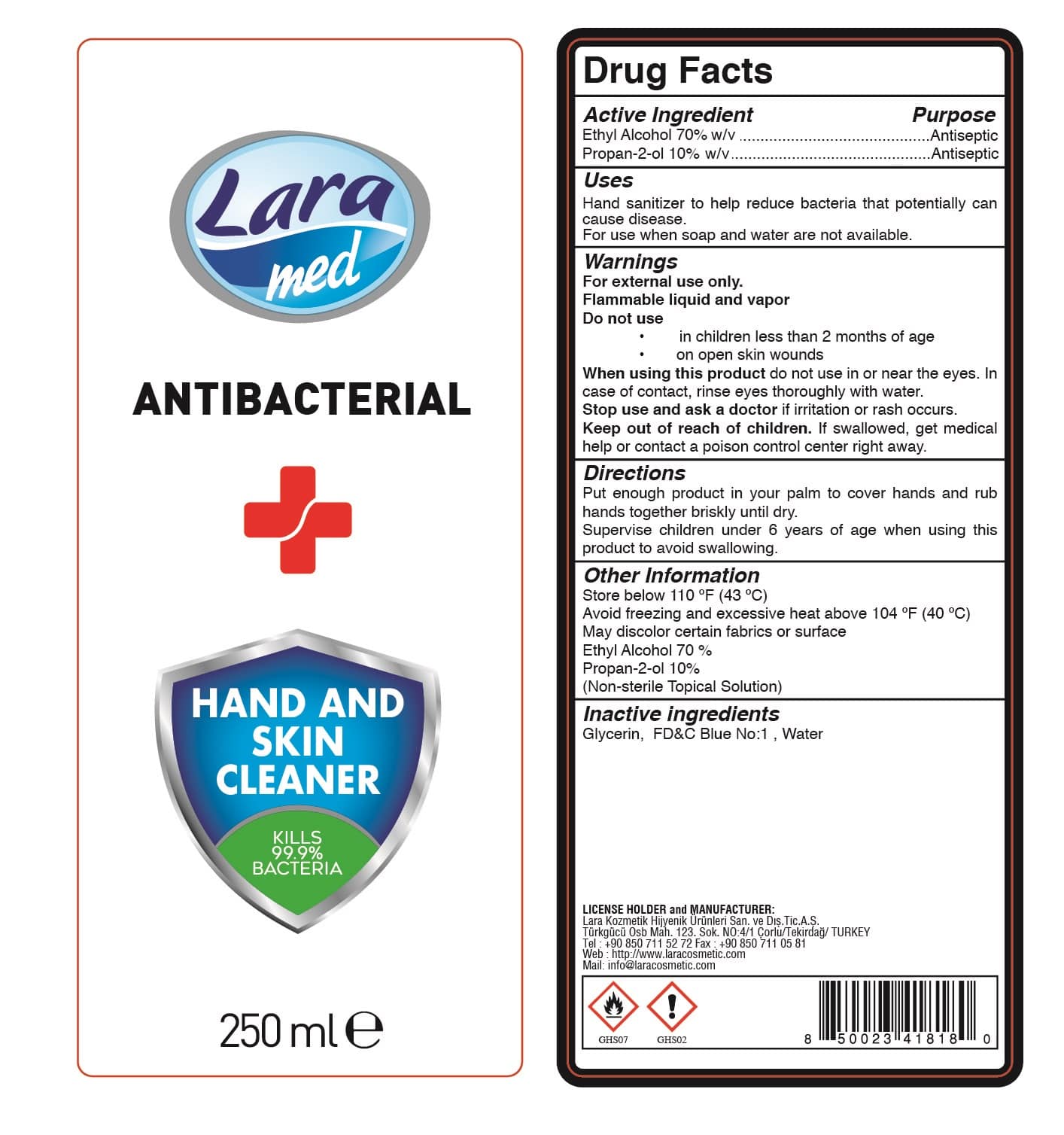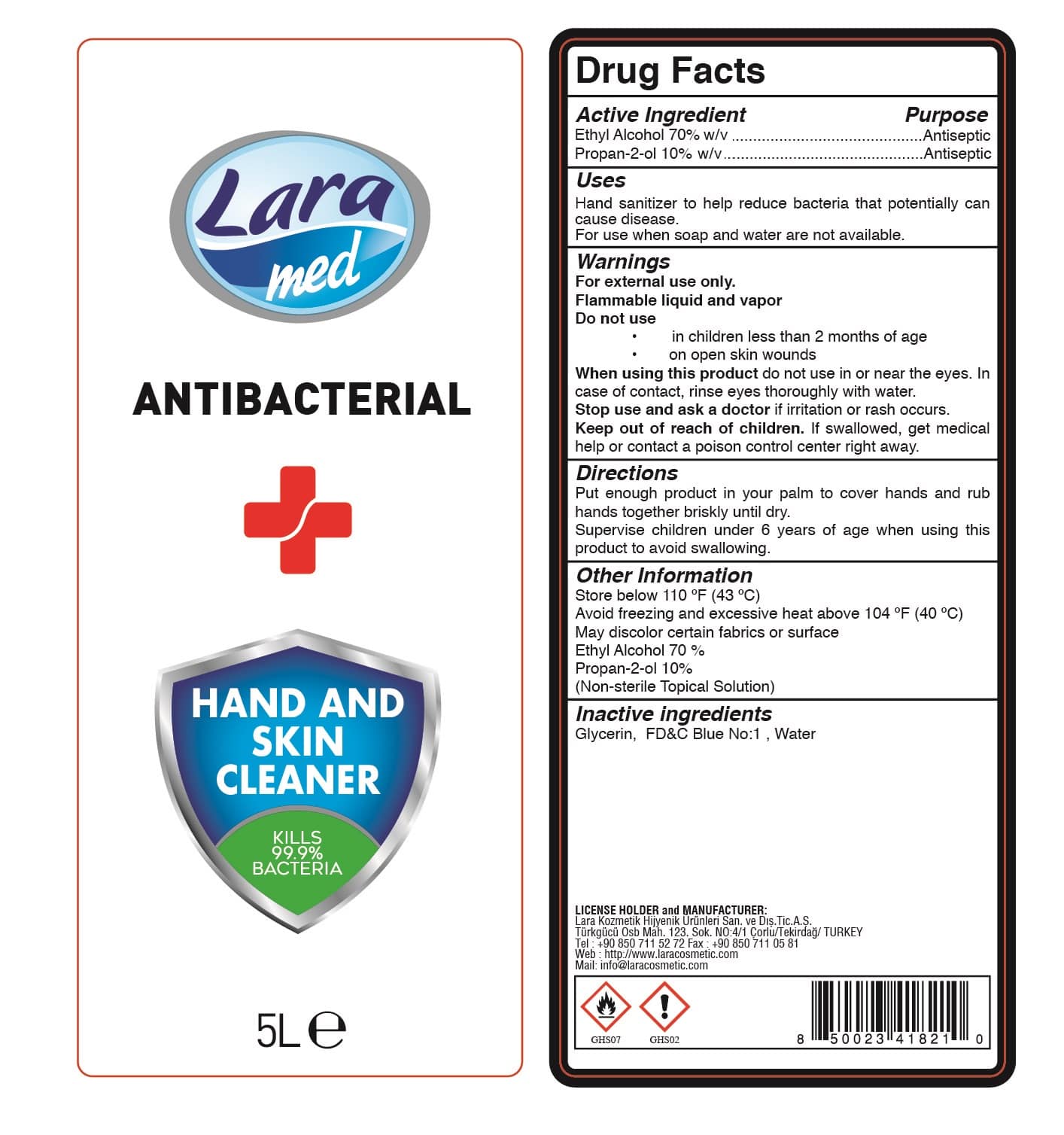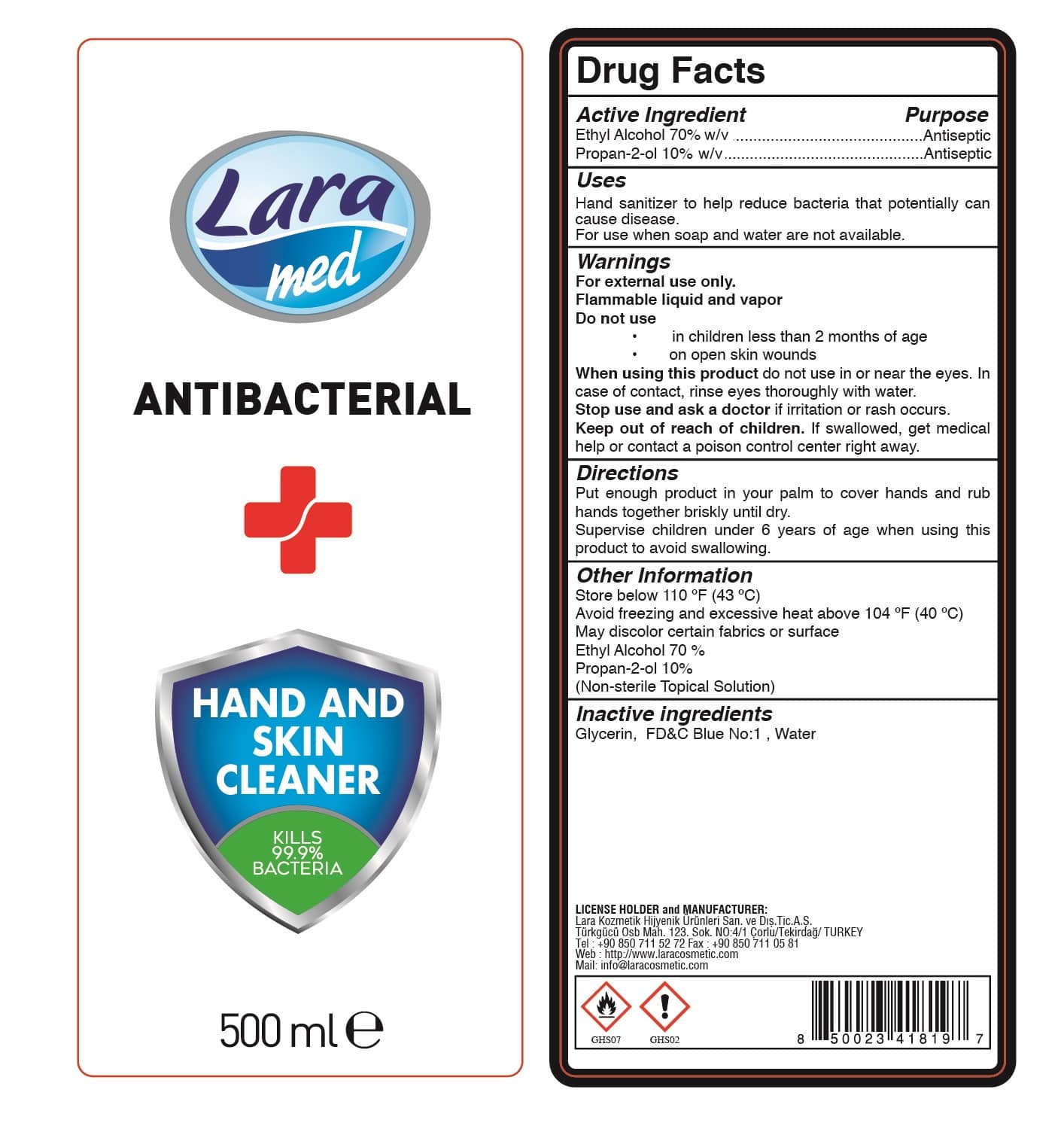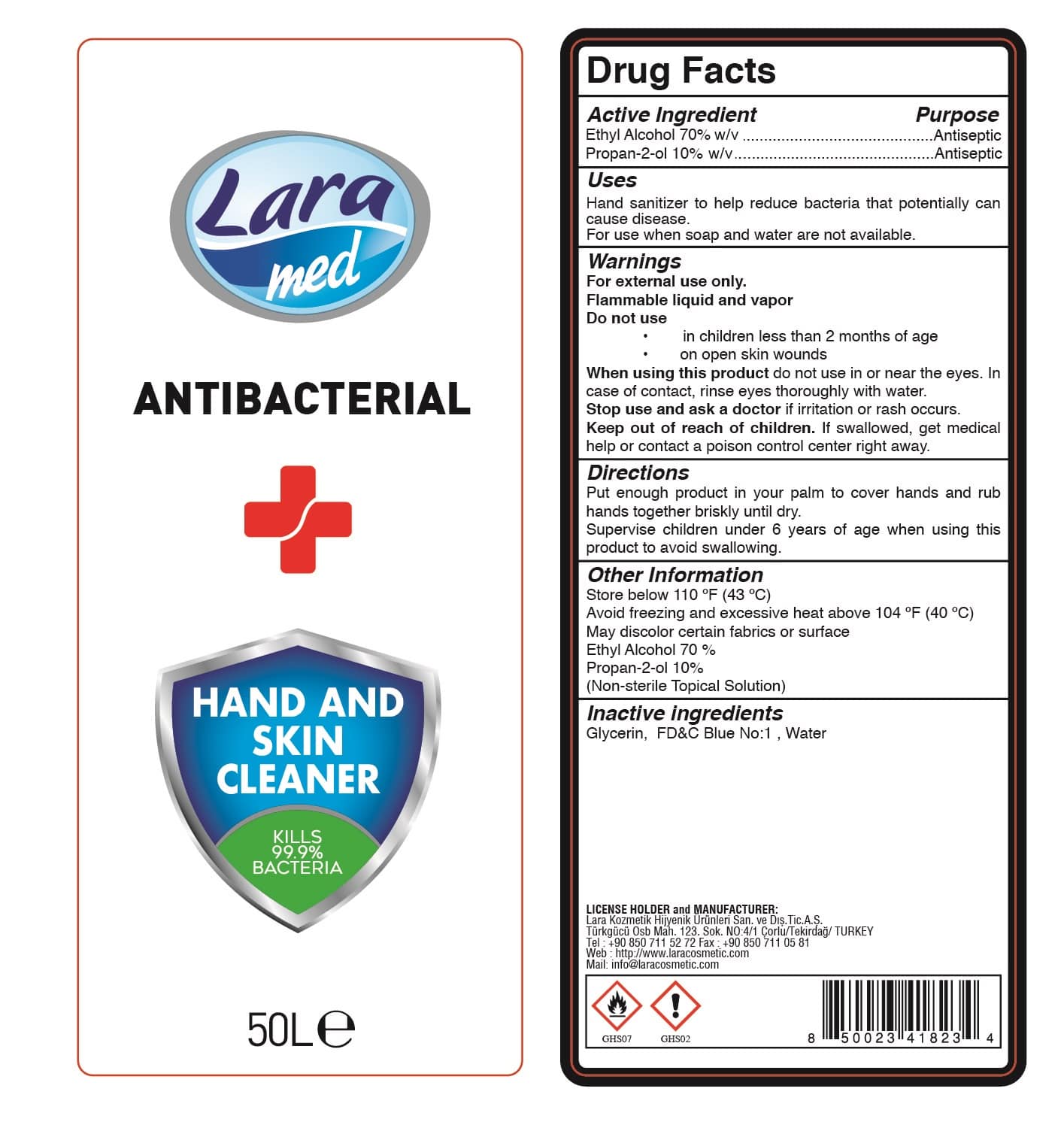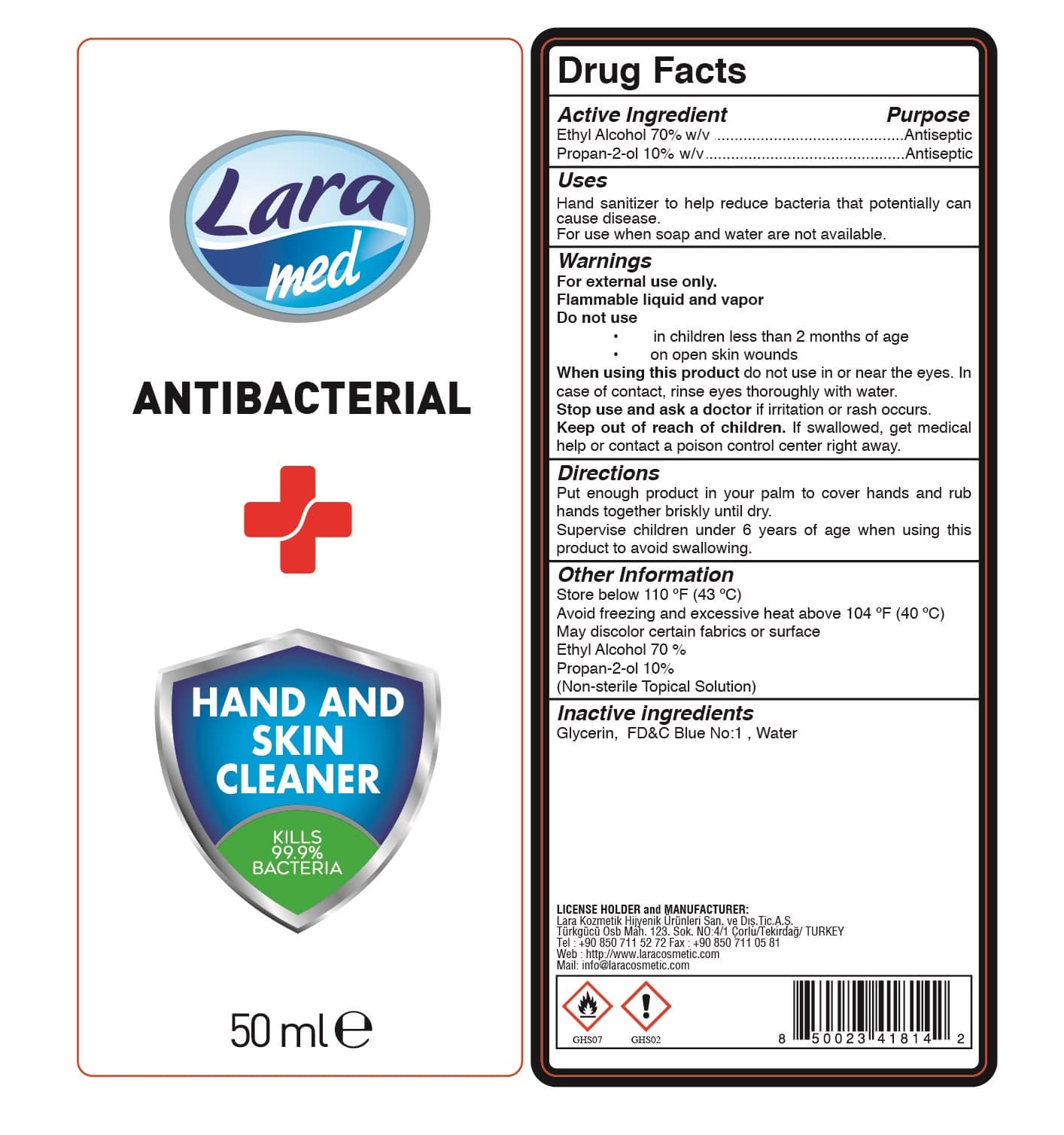 DRUG LABEL: LARA MED ANTIBACTERIAL HAND AND SKIN CLEANER
NDC: 86994-009 | Form: LIQUID
Manufacturer: LARA KOZMETIK HIJYENIK URUNLERI SANAYI VE DIS TICARET ANONIM SIRKETI
Category: otc | Type: HUMAN OTC DRUG LABEL
Date: 20201012

ACTIVE INGREDIENTS: ALCOHOL 70 g/100 mL; ISOPROPYL ALCOHOL 10 g/100 mL
INACTIVE INGREDIENTS: GLYCERIN; FD&C BLUE NO. 1; WATER

LARA MED ANTIBACTERIAL HAND AND SKIN CLEANER

This is a hand sanitizer manufactured according to the Temporary Policy for Preparation of Certain Alcohol-Based Hand Sanitizer Products During the Public Health Emergency (CoViD-19); Guidance for Industry.

The hand sanitizer is manufactured using only the following United States Pharmacopoeia (USP) grade ingredients in the preparation of the product (percentage in final product formulation) consistent with World Health Organization (WHO) recommendations:

Alcohol (ethanol) (USP or Food Chemical Codex (FCC) grade) (70%, volume/volume (w/v)) in an aqueous solution denatured according to Alcohol and Tobacco Tax and Trade Bureau regulations in 27 CFR part 20.
Propan-2-ol (10% w/v).
Glycerin
F&D C Blue No.1
Sterile distilled water or boiled cold water.

The firm does not add other active or inactive ingredients. Different or additional ingredients may impact the quality and potency of the product.

Active Ingredient(s)

Alcohol (ethanol)(70%, volume/volume (w/v))
Propan-2-ol (10% w/v).

Purpose: Antiseptic

Purpose

Antiseptic, Hand Sanitizer

Use

Hand Sanitizer to help reduce bacteria that potentially can cause disease. For use when soap and water are not available.

Warnings

For external use only. Flammable liquid and vapor

Do not use

- in children less than 2 months of age
- on open skin wounds

When using this product do not use in or near the eyes. In case of contact with eyes, rinse eyes thoroughly with water.
Stop use and ask a doctor if irritation or rash occurs. These may be signs of a serious condition.
Keep out of reach of children. If swallowed, get medical help or contact a Poison Control Center right away.

Stop use and ask a doctor if irritation or rash occurs. These may be signs of a serious condition.

Keep out of reach of children. If swallowed, get medical help or contact a Poison Control Center right away.

Directions

- Place enough product in your palm to cover hands and rub hands together briskly until dry.
- Supervise children under 6 years of age when using this product to avoid swallowing

Other information

Store between 110F (43 C)
Avoid freezing and excessive heat above 40C (104F)
May discolor certain fabrics or surface.
Ethyl Alcohol % 70
Porpan-2-ol %10

Non sterile topical solution

Inactive ingredients

glycerin, F&D C Blue No.1, purified water USP